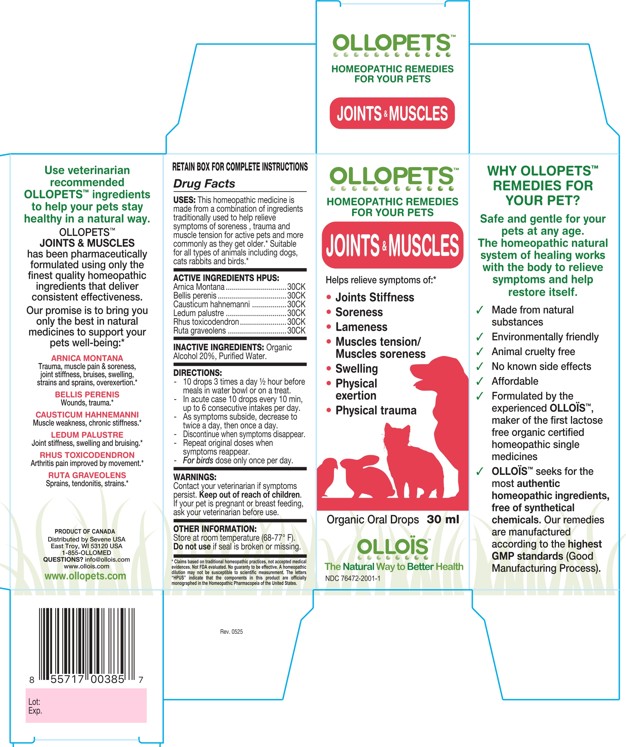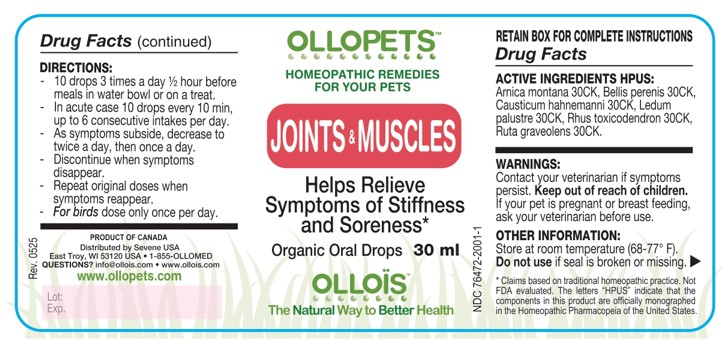 DRUG LABEL: OLLOPETS JOINTS AND MUSCLES
NDC: 76472-2001 | Form: SOLUTION
Manufacturer: SEVENE USA
Category: homeopathic | Type: OTC ANIMAL DRUG LABEL
Date: 20260217

ACTIVE INGREDIENTS: Arnica Montana 30 [hp_C]/100 mL; BELLIS PERENNIS 30 [hp_C]/100 mL; CAUSTICUM 30 [hp_C]/100 mL; RHODODENDRON TOMENTOSUM LEAFY TWIG 30 [hp_C]/100 mL; TOXICODENDRON PUBESCENS LEAF 30 [hp_C]/100 mL; RUTA GRAVEOLENS FLOWERING TOP 30 [hp_C]/100 mL
INACTIVE INGREDIENTS: ALCOHOL; WATER

SEVENE USA - OLLOPETS - JOINTS AND MUSCLES

ACTIVE INGREDIENT HPUS

Arnica Montana ..............................30CK
Bellis perenis ..................................30CK
Causticum hahnemanni .................30CK
Ledum palustre ..............................30CK
Rhus toxicodendron.......................30CK
Ruta graveolens .............................30CK